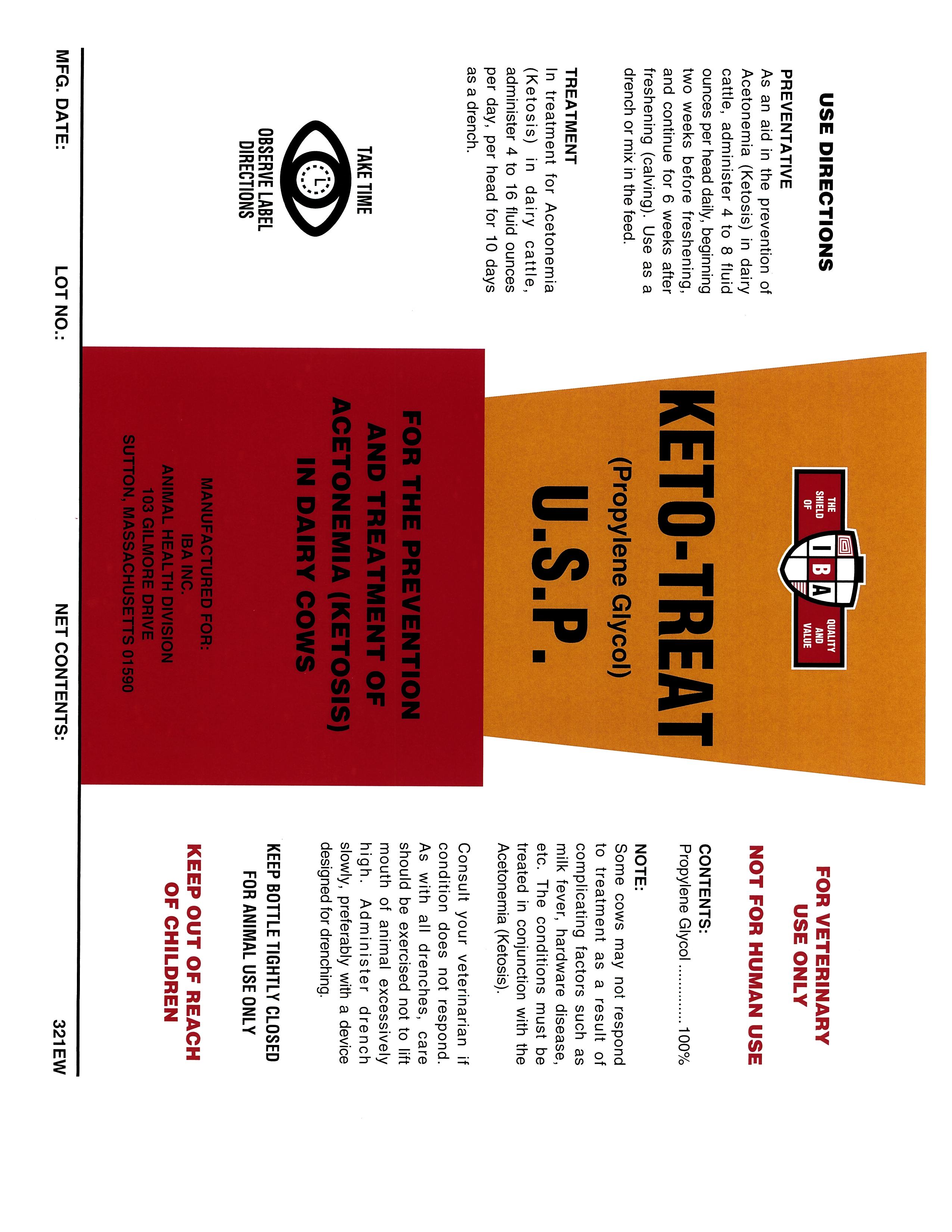 DRUG LABEL: KETO-TREAT
NDC: 29983-1038 | Form: LIQUID
Manufacturer: IBA
Category: animal | Type: OTC ANIMAL DRUG LABEL
Date: 20251209

ACTIVE INGREDIENTS: PROPYLENE GLYCOL 100 kg/100 kg

KETO-TREAT
(PROPYLENE GLYCOL)
U.S.P.

CONTENTS:

Propylene Glycol................................100%

USE DIRECTIONS:

PREVENTATIVE
As an aid in the prevention of Acetonemia (Ketosis) in dairy cattle, administer 4 to 8 fluid ounces per head daily, beginning two weeks before freshening, and continue for 6 weeks after freshening (calving). Use as a drench or mix in the feed.
TREATMENT
In treatment for Acetonemia (Ketosis) in dairy cattle, administer 4 to 16 fluid ounces per day, per head for 10 days as a drench.

GENERAL PRECAUTIONS

FOR VETINARY USE ONLY
NOT FOR HUMAN USE

NOTE:some cows may not respond to treatment as a result of complicating factors such as milk fever, hardware disease, etc. The conditions must be treated in conjunction with the Acetonemis (Ketosis).

Consult your veterinarian if condition does not respond. As with all drenches, care should be exercised not to lift mouth of animal excessively high. Administer drench slowly, preferably with a device designated with drenching.

KEEP BOTTLE TIGHTLY CLOSED FOR ANIMAL USE ONLY

KEEP OUT OF REACH OF CHILDREN